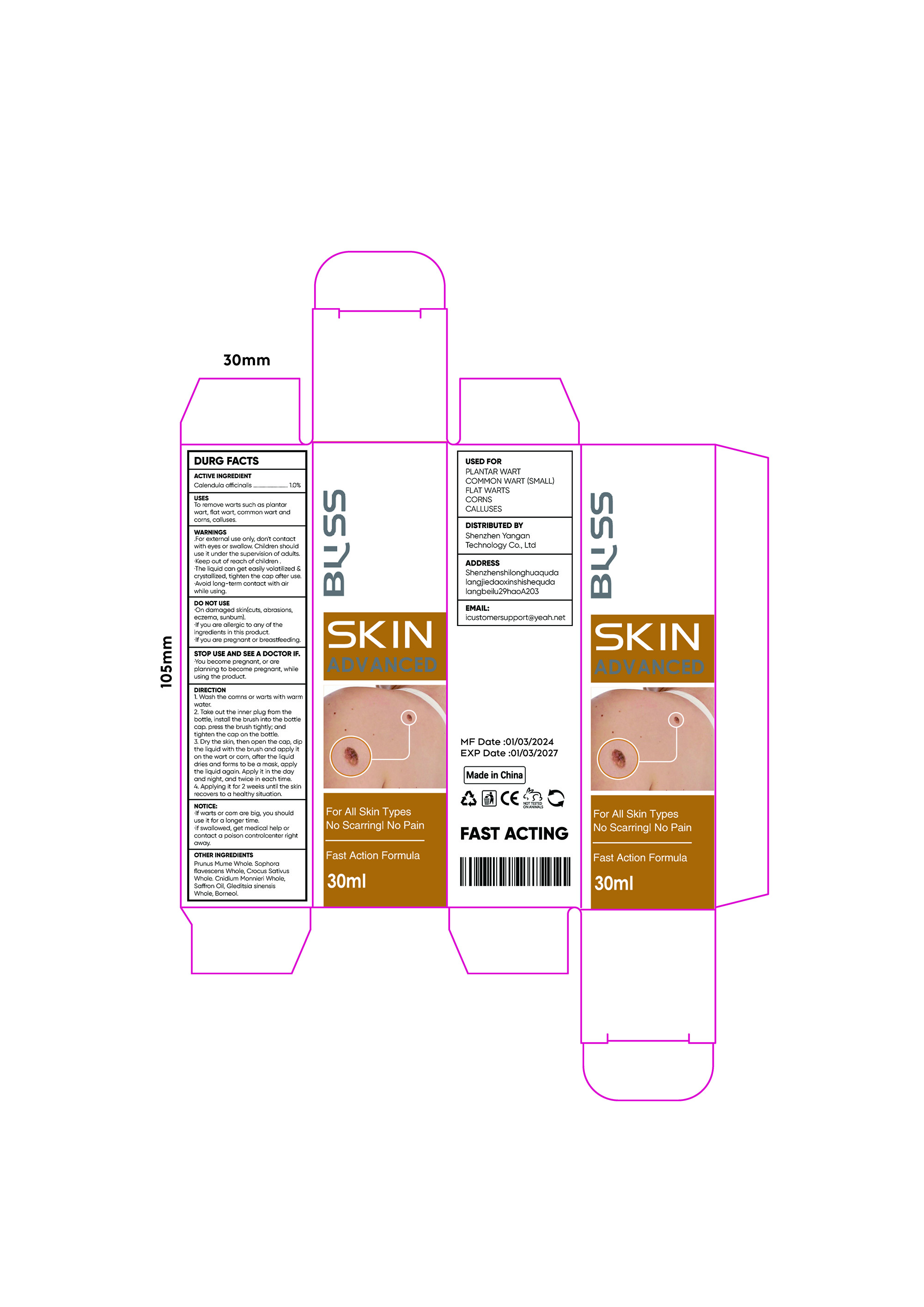 DRUG LABEL: Wart Remover
NDC: 84023-901 | Form: LIQUID
Manufacturer: Shenzhen Yangan Technology Co., Ltd.
Category: otc | Type: HUMAN OTC DRUG LABEL
Date: 20240424

ACTIVE INGREDIENTS: CALENDULA OFFICINALIS FLOWERING TOP 1 g/100 mL
INACTIVE INGREDIENTS: SAFFRON OIL; GLEDITSIA SINENSIS WHOLE; BORNEOL; CROCUS SATIVUS WHOLE; PRUNUS MUME WHOLE; SOPHORA FLAVESCENS WHOLE; CNIDIUM MONNIERI WHOLE

Wart Remover

Wart Remover

ACTIVE INGREDIENT

Calendula officinalis 1%

PURPOSE

To remove warts such as plantarwart, flat wart, common wart anacorns,calluses

INDICATIONS AND USAGE

To remove warts such as plantarwart, flat wart, common wart anacorns,calluses

WARNINGS

.For external use only, don't contactwith eyes or swallow. Children shoulduse it under the supervision of adultsKeep out of reach of childrenThe liquid can get easily volatilized &crystallized, tighten the cap after useAvoid long-term contact with airwhile using

DO NOT USE

On damaged skin(cuts, abrasionseczema, sunbum)lf you are allergic to any of theingredients in this product.lf you are pregnant or breastfeeding

WHEN USING

For external use only, don't contactwith eyes or swallow. Children shoulduse it under the supervision of adultsKeep out of reach of childrenThe liquid can get easily volatilized &crystallized, tighten the cap after useAvoid long-term contact with airwhile using

STOP USE

You become pregnant, or areplanning to become pregnant, whileusing the product.

Keep out of reach of children

DOSAGE AND ADMINISTRATION

1.Wash the comns or warts with warm water.
2. Take out the inner plug from thebottle, install the brush into the bottlecap. press the brush tightly; andtighten the cap on the bottle.
3. Dry the skin, then open the cap, dipthe liquid with the brush and apply iton the wart or corn, after the liquiddries and forms to be a mask, applythe liquid again. Apply it in the dayand night, and twice in each time
4. Applying it for 2 weeks until the skinrecovers to a healthy situation.

INACTIVE INGREDIENT

Prunus Mume Whole
Sophora flavescens Whole
Crocus Sativus Whole
Cnidium Monnieri Whole
Saffron Oil
Gleditsia sinensis Whole
Borneol